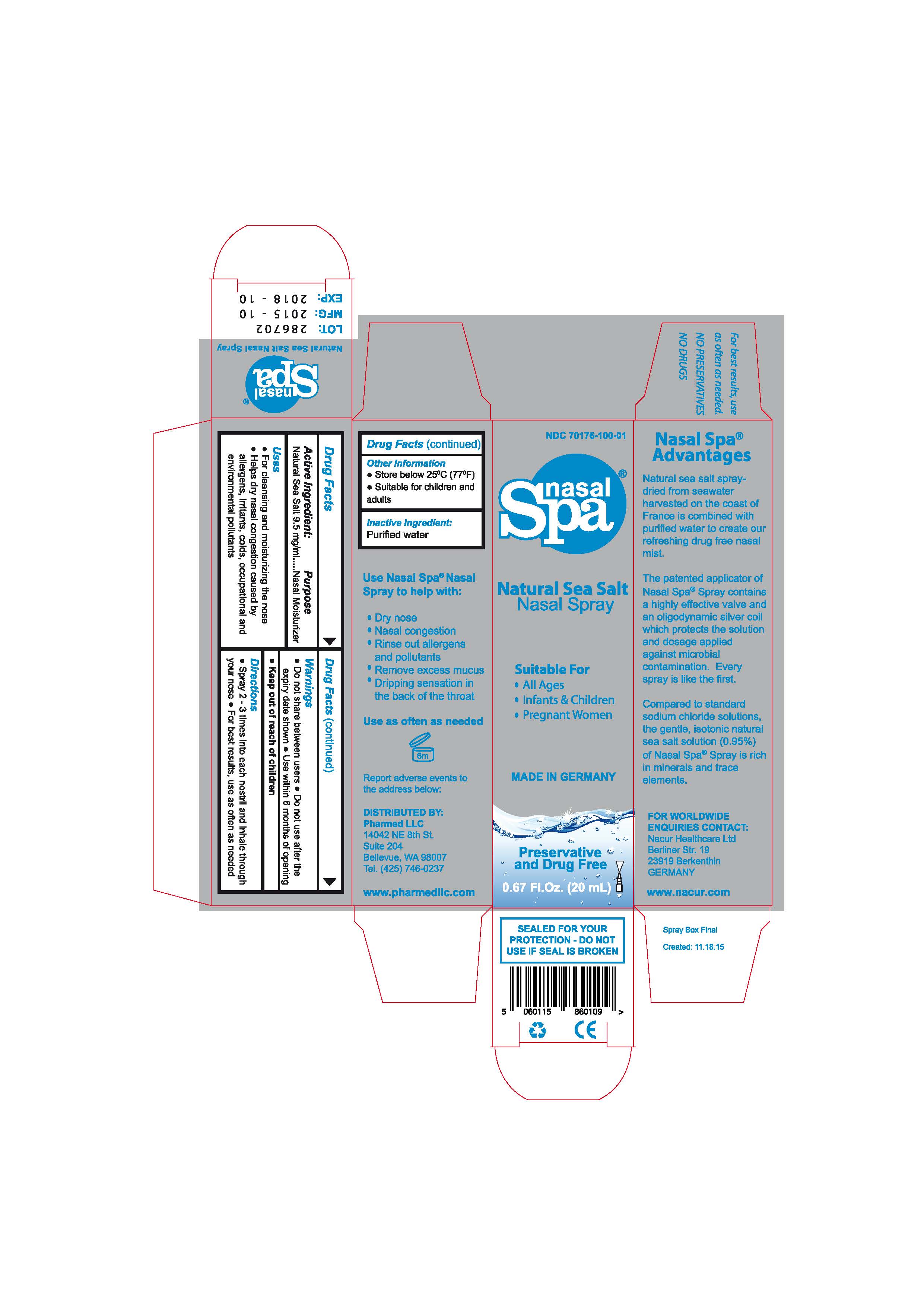 DRUG LABEL: Nasal Spa
NDC: 70176-100 | Form: SPRAY
Manufacturer: NACUR HEALTHCARE LTD
Category: otc | Type: HUMAN OTC DRUG LABEL
Date: 20160424

ACTIVE INGREDIENTS: SODIUM CHLORIDE 9.5 mg/1 mL
INACTIVE INGREDIENTS: WATER

Drug Facts

Active Ingredient:

Natural Sea Salt 9.5 mg/mL

Purpose

Nasal Moisturizer

Uses

-For cleansing and moisturizing the nose

-Helps dry nasal congestion caused by

allergens, irritants, colds, occupational and

environmental pollutants

Warnings

-Do not share between users -Do not use after the

expiry date -Use within 6 months of opening

Keep out of reach of children

Directions

-Spray 2 - 3 times into each nostril and inhale through

your nose -For best results, use as often as needed

Other Information

-Store below 25C (77F)

-Suitable for children and

adults

Inactive Ingredient

Purified water

DESCRIPTION

For expiry date see top lid.

Use Nasal Spa Nasal Spray

to help:

- nasal congestion
- dry nose
- runny clear mucus
- rinse out allergens and pollutants
- remove excess mucus
- dripping sensation in the back of the throat

DESCRIPTION

The patented applicator of

the Nasal Spa Nasal Spray

contains an highly effective

valve and an oligo-

dynamically active silver coil

which protects the solution

and the dosage applied

against microbial

congestion.

The sea salt is manufactured

in a highly technical

process (spray-drying)

harvesting seawater taken

from an archipelago off

the coast of France in Europe.

Compared to standard

sodium chloride solutions,

the gentle, isotonic natural

sea salt solution (0.95%) of

the Nasal Spa Spray is

rich in minerals and trace

elements.

MADE IN GERMANY